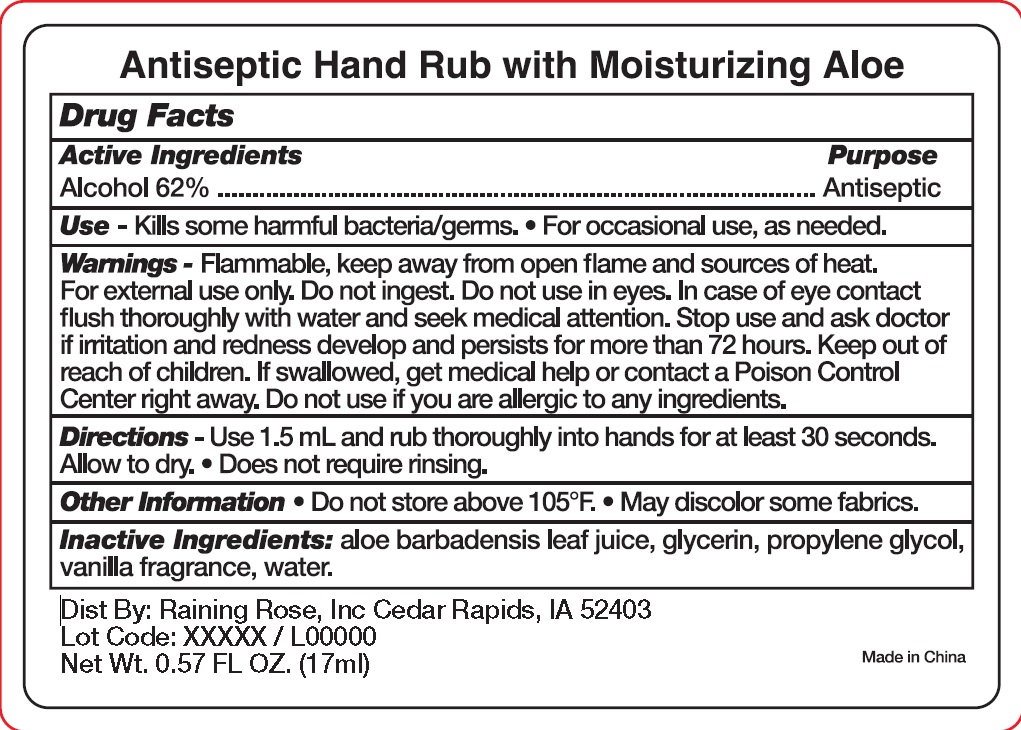 DRUG LABEL: Hand Sanitizer
NDC: 65692-1003 | Form: GEL
Manufacturer: Raining Rose, Inc.
Category: otc | Type: HUMAN OTC DRUG LABEL
Date: 20250407

ACTIVE INGREDIENTS: ALCOHOL 62 mL/100 mL
INACTIVE INGREDIENTS: WATER; ALOE VERA LEAF; GLYCERIN; PROPYLENE GLYCOL

65692-1003

Active Ingredients
Alcohol 62%

Purpose
Antiseptic

Warnings

Flammable, keep away from open flame and sources of heat. For external use only. Do not ingest.

Do not use in eyes. In case of eye contact flush thoroughly with water and seek medical attention.

Stop use and ask doctor if irritation and redness develops and persists for more than 72 hours. Do not use if you are allergic to any ingredients.

Keep out of reach of children. If swallowed, get medical help or contact a Poison Control Center right away.

Directions

- Use 1.5mL and rub thoroughly into hands for at least 30 seconds. Allow to dry.
- Does not require rinsing.

INACTIVE INGREDIENT

Inactive Ingredients: Aloe Barbadenis Leaf Juice, Glycerin, Propylene Glycol, Vanilla Fragrance, Water.

Use

- Kills some harmful bacteria/germs.
- For occasional use, as needed.

Other Information

- Do not store above 105 F
- May discolor some fabrics.